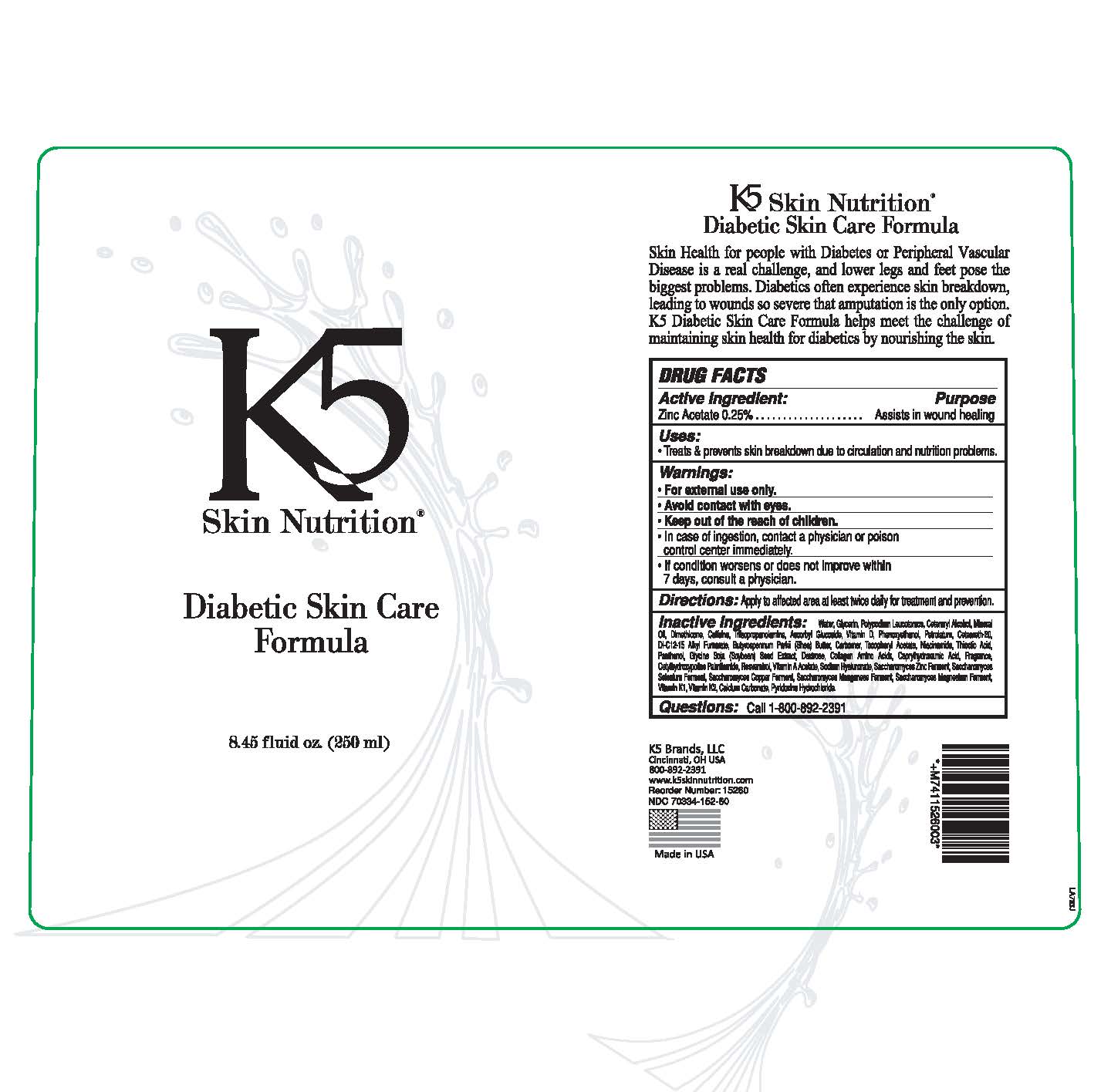 DRUG LABEL: DIABETIC SKIN CARE FORMULA
NDC: 70334-152 | Form: SOAP
Manufacturer: K5 BRANDS, LLC
Category: otc | Type: HUMAN OTC DRUG LABEL
Date: 20200131

ACTIVE INGREDIENTS: ZINC ACETATE 0.0025 mg/1 mg
INACTIVE INGREDIENTS: DI-C12-15 ALKYL FUMARATE; PETROLATUM; MINERAL OIL; NIACINAMIDE; WATER; .ALPHA.-LIPOIC ACID; SHEA BUTTER; .ALPHA.-TOCOPHEROL ACETATE; SOYBEAN; HYALURONIC ACID; HYALURONATE SODIUM; DEXTROSE; PANTHENOL; PYRIDOXINE HYDROCHLORIDE; VITAMIN A ACETATE; VITAMIN D; DIMETHICONE; CETOSTEARYL ALCOHOL; POLYOXYL 20 CETOSTEARYL ETHER; CETYLHYDROXYPROLINE PALMITAMIDE

PURPOSE

Assist in wound healing

ACTIVE INGREDIENT

Zinc Acetate .............25%

INACTIVE INGREDIENTS

CETEARYL ALCOHOL
POLYOXYL 20 CETOSTEARYL ETHER
DI-C12-15 ALKYL FUMARATE
PETROLATUM
MINERAL OIL
SHEA BUTTER
DIMETHICONE
CETYLHYDROXYPROLINE PALMITAMIDE
ALPHA LIPOIC ACID
WATER
CARBOMER HOMOPOLYMER
NIACINAMIDE
TOCOPHERYL ACETATE
SOYBEAN

HYALURONIC ACID
HYALURONATE SODIUM
DEXTROSE
PANTHENOL
PYRIDOXINE HYDROCHLORIDE
VITAMIN A ACETATE
VITAMIN D

INDICATIONS AND USAGE

Treats and prevents skin breakdown due to circulation and nutrition problems

DOSAGE AND ADMINISTRATION

Apply to affected area at least twice daily for treatment and prevention

WARNINGS

For external use only.

Avoid contact with eyes.

In case of indegestion contact a poison control center or physician immediately

If condition worsens or does not improve within 7 days, consult physician.

KEEP OUT OF REACH OF CHILDREN